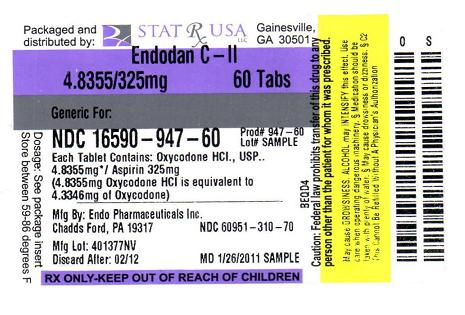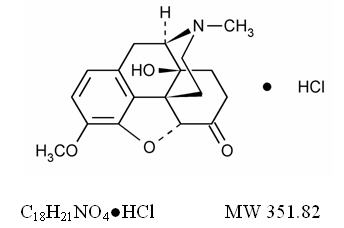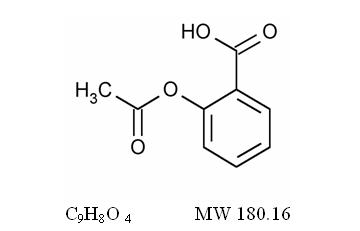 DRUG LABEL: ENDODAN
NDC: 16590-947 | Form: TABLET
Manufacturer: STAT RX USA LLC
Category: prescription | Type: HUMAN PRESCRIPTION DRUG LABEL
Date: 20110523
DEA Schedule: CII

ACTIVE INGREDIENTS: OXYCODONE HYDROCHLORIDE 4.8355 mg/1 1; ASPIRIN 325 mg/1 1
INACTIVE INGREDIENTS: D&C YELLOW NO. 10; FD&C YELLOW NO. 6; CELLULOSE, MICROCRYSTALLINE; STARCH, CORN

DESCRIPTION

Each ENDODAN Tablet contains:

Oxycodone Hydrochloride, USP 4.8355 mg 1

Aspirin, USP 325 mg

ENDODAN Tablets also contain the following inactive ingredients: D and C Yellow 10, FD and C Yellow 6, microcrystalline cellulose and corn starch.

The oxycodone hydrochloride component is Morphinan-6-one, 4,5-epoxy-14-hydroxy-3-methoxy-17-methyl-, hydrochloride, (5a)-., a white to off-white, hygroscopic crystals or powder, odorless, soluble in water; slightly soluble in alcohol and is represented by the following structural formula:

The aspirin component is 2-(acetyloxy)-, Benzoic acid, a white crystal, commonly tabular or needle-like, or white, crystalline powder. Is odorless or has a faint odor. Is stable in dry air; in moist air it gradually hydrolyzes to salicylic and acetic acids. Slightly soluble in water; freely soluble in alcohol; soluble in chloroform and in ether; sparingly soluble in absolute ether and is represented by the following structural formula:

1 4.8355 mg oxycodone HCl is equivalent to 4.3346 mg of oxycodone as the free base.

CLINICAL PHARMACOLOGY

Central Nervous System

Oxycodone is a semisynthetic pure opioid agonist whose principal therapeutic action is analgesia. Other pharmacological effects of oxycodone include anxiolysis, euphoria and feelings of relaxation. These effects are mediated by receptors (notably μ and κ) in the central nervous system for endogenous opioid-like compounds such as endorphins and enkephalins. Oxycodone produces respiratory depression through direct activity at respiratory centers in the brain stem and depresses the cough reflex by direct effect on the center of the medulla.

Aspirin (acetylsalicylic acid) works by inhibiting the body’s production of prostaglandins, including prostaglandins involved in inflammation. Prostaglandins cause pain sensations by stimulating muscle contractions and dilating blood vessels throughout the body. In the CNS, aspirin works on the hypothalamus heat-regulating center to reduce fever, however, other mechanisms may be involved.

Gastrointestinal Tract and Other Smooth Muscle

Oxycodone reduces motility by increasing smooth muscle tone in the stomach and duodenum. In the small intestine, digestion of food is delayed by decreases in propulsive contractions. Other opioid effects include contraction of biliary tract smooth muscle, spasm of the Sphincter of Oddi, increased ureteral and bladder sphincter tone, and a reduction in uterine tone.

Aspirin can produce gastrointestinal injury (lesions, ulcers) through a mechanism that is not yet completely understood, but may involve a reduction in eicosanoid synthesis by the gastric mucosa. Decreased production of prostaglandins may compromise the defenses of the gastric mucosa and the activity of substances involved in tissue repair and ulcer healing.

Cardiovascular System

Oxycodone may produce a release of histamine and may be associated with orthostatic hypotension, and other symptoms, such as pruritus, flushing, red eyes, and sweating.

Platelet Aggregation

Aspirin affects platelet aggregation by irreversibly inhibiting prostaglandin cyclo-oxygenase. This effect lasts for the life of the platelet and prevents the formation of the platelet aggregating factor thromboxane A2. Nonacetylated salicylates do not inhibit this enzyme and have no effect on platelet aggregation. At somewhat higher doses, aspirin reversibly inhibits the formation of prostaglandin 12 (prostacyclin), which is an arterial vasodilator and inhibits platelet aggregation.

Pharmacokinetics

Absorption and Distribution

The mean absolute oral bioavailability of oxycodone in cancer patients was reported to be about 87%. Oxycodone has been shown to be 45% bound to human plasma proteins in vitro. The volume of distribution after intravenous administration is 211.9 ±186.6 L.

Aspirin is hydrolyzed primarily to salicylic acid in the gut wall and during first-pass metabolism through the liver. Salicylic acid is absorbed rapidly from the stomach, but most of the absorption occurs in the proximal small intestine. Following absorption, salicylate is distributed to most body tissues and fluids, including fetal tissues, breast milk, and the CNS. High concentrations are found in the liver and kidneys. Salicylate is variably bound to serum proteins, particularly albumin.

Metabolism and Elimination

A high portion of oxycodone is N-dealkylated to noroxycodone during first-pass metabolism. Oxymorphone, is formed by the O-demethylation of oxycodone. The metabolism of oxycodone to oxymorphone is catalyzed by CYP2D6. Free and conjugated noroxycodone, free and conjugated oxycodone, and oxymorphone are excreted in human urine following a single oral dose of oxycodone. Approximately 8% to 14% of the dose is excreted as free oxycodone over 24 hours after administration. Following a single, oral dose of oxycodone, the mean ± SD elimination half-life is 3.51 ± 1.43 hours.

The biotransformation of aspirin occurs primarily in the liver by the microsomal enzyme system. With a plasma half-life of approximately 15 minutes, aspirin is rapidly hydrolyzed to salicylate. At low doses, salicylate elimination follows first-order kinetics. The plasma half-life of salicylate is approximately 2 to 3 hours.

Approximately 10% of aspirin is excreted as unchanged salicylate in the urine. The major metabolites excreted in the urine are salicyluric acid (75%), salicyl phenolic glucuronide (10%), salicyl acyl glucuronide (5%), and gentisic and gentisuric acid (less than 1%) each. Eighty to 100% of a single dose is excreted in the urine within 24 to 72 hours.

INDICATIONS AND USAGE

ENDODAN tablets are indicated for the management of moderate to moderately severe pain.

CONTRAINDICATIONS

ENDODAN tablets are contraindicated in patients with known hypersensitivity to oxycodone or aspirin, and in any situation where opioids or aspirin are contraindicated. Aspirin is contraindicated for patients with hemophilia.

Reye Syndrome: Aspirin should not be used in children or teenagers for viral infections, with or without fever, because of the risk of Reye syndrome with concomitant use of aspirin in certain viral illnesses.

Allergy: Aspirin is contraindicated in patients with known allergy to nonsteroidal anti-inflammatory drug products and in patients with the syndrome of asthma, rhinitis, and nasal polyps. Aspirin may cause severe urticaria, angioedema, or bronchospasm (asthma).

Oxycodone is contraindicated in patients with known hypersensitivity to oxycodone. Oxycodone is contraindicated in any situation where opioids are contraindicated including patients with significant respiratory depression (in unmonitored settings or the absence of resuscitative equipment) and patients with acute or severe bronchial asthma or hypercarbia. Oxycodone is contraindicated in the setting of suspected or known paralytic ileus.

WARNINGS

Misuse, Abuse and Diversion of Opioids

Oxycodone is an opioid agonist of the morphine-type. Such drugs are sought by drug abusers and people with addiction disorders and are subject to criminal diversion.

Oxycodone can be abused in a manner similar to other opioid agonists, legal or illicit. This should be considered when prescribing or dispensing ENDODAN tablets in situations where the physician or pharmacist is concerned about an increased risk of misuse, abuse, or diversion. Concerns about misuse, addiction, and diversion should not prevent the proper management of pain.

Healthcare professionals should contact their State Professional Licensing Board, or State Controlled Substances Authority for information on how to prevent and detect abuse or diversion of this product.

Administration of ENDODAN (Oxycodone and Aspirin Tablets, USP) tablets should be closely monitored for the following potentially serious adverse reactions and complications:

Respiratory Depression

Respiratory depression is a hazard with the use of oxycodone, one of the active ingredients in ENDODAN tablets, as with all opioid agonists. Elderly and debilitated patients are at particular risk for respiratory depression as are non-tolerant patients given large initial doses of oxycodone or when oxycodone is given in conjunction with other agents that depress respiration. Oxycodone should be used with extreme caution in patients with acute asthma, chronic obstructive pulmonary disorder (COPD), cor pulmonale, or preexisting respiratory impairment. In such patients, even usual therapeutic doses of oxycodone may decrease respiratory drive to the point of apnea. In these patients alternative non-opioid analgesics should be considered, and opioids should be employed only under careful medical supervision at the lowest effective dose.

In case of respiratory depression, a reversal agent such as naloxone hydrochloride may be utilized (see OVERDOSAGE).

Head Injury and Increased Intracranial Pressure

The respiratory depressant effects of opioids include carbon dioxide retention and secondary elevation of cerebrospinal fluid pressure, and may be markedly exaggerated in the presence of head injury, other intracranial lesions or a pre-existing increase in intracranial pressure. Oxycodone produces effects on pupillary response and consciousness which may obscure neurologic signs of worsening in patients with head injuries.

Hypotensive Effect

Oxycodone may cause severe hypotension particularly in individuals whose ability to maintain blood pressure has been compromised by a depleted blood volume, or after concurrent administration with drugs which compromise vasomotor tone such as phenothiazines. Oxycodone, like all opioid analgesics of the morphine-type, should be administered with caution to patients in circulatory shock, since vasodilation produced by the drug may further reduce cardiac output and blood pressure. Oxycodone may produce orthostatic hypotension in ambulatory patients.

Alcohol Warning

Patients who consume three or more alcoholic drinks every day should be counseled about the bleeding risks involved with chronic, heavy alcohol use while taking aspirin.

Coagulation Abnormalities

Even low doses of aspirin can inhibit platelet function leading to an increase in bleeding time. This can adversely affect patients with inherited (hemophilia) or acquired (liver disease or vitamin K deficiency) bleeding disorders.

GI Side Effects

GI side effects include stomach pain, heartburn, nausea, vomiting, and gross GI bleeding. Although minor upper GI symptoms, such as dyspepsia, are common and can occur anytime during therapy, physicians should remain alert for signs of ulceration and bleeding, even in the absence of previous GI symptoms. Physicians should inform patients about the signs and symptoms of GI side effects and what steps to take if they occur.

Peptic Ulcer Disease

Patients with a history of active peptic ulcer disease should avoid using aspirin, which can cause gastric mucosal irritation and bleeding.

PRECAUTIONS

General

Opioid analgesics should be used with caution when combined with CNS depressant drugs, and should be reserved for cases where the benefits of opioid analgesia outweigh the known risks of respiratory depression, altered mental state, and postural hypotension.

ENDODAN tablets should be given with caution to patients with CNS depression, elderly or debilitated patients, patients with severe impairment of hepatic, pulmonary, or renal function, hypothyroidism, Addison's disease, prostatic hypertrophy, urethral stricture, acute alcoholism, delirium tremens, kyphoscoliosis with respiratory depression, myxedema, and toxic psychosis.

ENDODAN tablets may obscure the diagnosis or clinical course in patients with acute abdominal conditions. Oxycodone may aggravate convulsions in patients with convulsive disorders, and all opioids may induce or aggravate seizures in some clinical settings.

Following administration of ENDODAN tablets, anaphylactic reactions have been reported in patients with a known hypersensitivity to codeine, a compound with a structure similar to morphine and oxycodone. The frequency of this possible cross-sensitivity is unknown.

Aspirin has been associated with elevated hepatic enzymes, blood urea nitrogen and serum creatinine, hyperkalemia, proteinuria, and prolonged bleeding time.

Hemorrhage

Aspirin may increase the likelihood of hemorrhage due to its effect on the gastric mucosa and platelet function (prolongation of bleeding time). Salicylates should be used with caution in the presence of peptic ulcer or coagulation abnormalities.

Pregnancy

Aspirin can cause fetal harm when administered to a pregnant woman. Salicylates readily cross the placenta and by inhibiting prostaglandin synthesis, may cause constriction of ductus arteriosus, resulting in pulmonary hypertension and increased fetal mortality and, possibly other untoward fetal effects. Aspirin use in pregnancy can also result in alteration in maternal and neonatal hemostasis mechanisms. Maternal aspirin use during later stages of pregnancy may cause low birth weight, increased incidence of intracranial hemorrhage in premature infants, stillbirths and neonatal death. The use of aspirin during pregnancy especially in the third trimester should be avoided. If ENDODAN tablets are used during pregnancy, or if the patient becomes pregnant while taking this drug, the patient should be apprised of the potential hazard to the fetus.

Renal Failure

Avoid aspirin in patients with severe renal failure (glomerular filtration rate less than 10 mL/minute).

Hepatic Insufficiency

Avoid aspirin in patients with severe hepatic insufficiency.

Interactions with Other CNS Depressants

Patients receiving other opioid analgesics, general anesthetics, phenothiazines, other tranquilizers, centrally-acting anti-emetics, sedative-hypnotics or other CNS depressants (including alcohol) concomitantly with ENDODAN tablets may exhibit an additive CNS depression. When such combined therapy is contemplated, the dose of one or both agents should be reduced.

Interactions with Mixed Agonist/Antagonist Opioid Analgesics

Agonist/antagonist analgesics (i.e., pentazocine, nalbuphine, and butorphanol) should be administered with caution to a patient who has received or is receiving a course of therapy with a pure opioid agonist analgesic such as oxycodone. In this situation, mixed agonist/antagonist analgesics may reduce the analgesic effect of oxycodone and/or may precipitate withdrawal symptoms in these patients.

Ambulatory Surgery and Postoperative Use

Oxycodone and other morphine-like opioids have been shown to decrease bowel motility. Ileus is a common postoperative complication, especially after intra-abdominal surgery with use of opioid analgesia. Caution should be taken to monitor for decreased bowel motility in postoperative patients receiving opioids. Standard supportive therapy should be implemented.

Use in Pancreatic/Biliary Tract Disease

Oxycodone may cause spasm of the sphincter of Oddi and should be used with caution in patients with biliary tract disease, including acute pancreatitis. Opioids like oxycodone may cause increases in the serum amylase level.

Tolerance and Physical Dependence

Tolerance is the need for increasing doses of opioids to maintain a defined effect such as analgesia (in the absence of disease progression or other external factors). Physical dependence is manifested by withdrawal symptoms after abrupt discontinuation of a drug or upon administration of an antagonist. Physical dependence and tolerance are not unusual during chronic opioid therapy.

The opioid abstinence or withdrawal syndrome is characterized by some or all of the following: restlessness, lacrimation, rhinorrhea, yawning, perspiration, chills, myalgia, and mydriasis. Other symptoms also may develop, including: irritability, anxiety, backache, joint pain, weakness, abdominal cramps, insomnia, nausea, anorexia, vomiting, diarrhea, or increased blood pressure, respiratory, respiratory rate, or heart rate.

In general, opioids should not be abruptly discontinued (see DOSAGE AND ADMINISTRATION: Cessation of Therapy).

Information for Patients/Caregivers

The following information should be provided to patients receiving ENDODAN tablets by their physician, nurse, pharmacist, or caregiver:

1. Patients should be aware that ENDODAN tablets contain oxycodone, which is a morphine-like substance.
2. Patients should be instructed to keep ENDODAN tablets in a secure place out of the reach of children. In the case of accidental ingestions, emergency medical care should be sought immediately.
3. When ENDODAN tablets are no longer needed, the unused tablets should be destroyed by flushing down the toilet.
4. Patients should be advised not to adjust the medication dose themselves. Instead, they must consult with their prescribing physician.
5. Patients should be advised that ENDODAN tablets may impair mental and/or physical ability required for the performance of potentially hazardous tasks (e.g., driving, operating heavy machinery).
6. Patients should not combine ENDODAN tablets with alcohol, opioid analgesics, tranquilizers, sedatives, or other CNS depressants unless under the recommendation and guidance of a physician. When co-administered with another CNS depressant, ENDODAN tablets can cause dangerous additive central nervous system or respiratory depression, which can result in serious injury or death.
7. The safe use of ENDODAN tablets during pregnancy has not been established; thus, women who are planning to become pregnant or are pregnant should consult with their physician before taking ENDODAN tablets.
8. Nursing mothers should consult with their physicians about whether to discontinue nursing or discontinue ENDODAN tablets because of the potential for serious adverse reactions to nursing infants.
9. Patients who are treated with ENDODAN tablets for more than a few weeks should be advised not to abruptly discontinue the medication. Patients should consult with their physician for a gradual discontinuation dose schedule to taper off the medication.
10. Patients should be advised that ENDODAN tablets are a potential drug of abuse. They should protect it from theft, and it should never be given to anyone other than the individual for whom it was prescribed.
11. Patients should be advised that ENDODAN tablets may cause or worsen constipation. They should discuss any past history of constipation with their prescribing physician so a management plan may be initiated.

Laboratory Tests

Although oxycodone may cross-react with some drug urine tests, no available studies were found which determined the duration of detectability of oxycodone in urine drug screens. However, based on pharmacokinetic data, the approximate duration of detectability for a single dose of oxycodone is roughly estimated to be one to two days following drug exposure.

Urine testing for opiates may be performed to determine illicit drug use and for medical reasons such as evaluation of patients with altered states of consciousness or monitoring efficacy of drug rehabilitation efforts. The preliminary identification of opiates in urine involves the use of an immunoassay screening and thin-layer chromatography (TLC). Gas chromatography/mass spectrometry (GC/MS) may be utilized as a third-stage identification step in the medical investigational sequence for opiate testing after immunoassay and TLC. The identities of 6-keto opiates (e.g., oxycodone) can further be differentiated by the analysis of their methoxime-trimethylsilyl (MO-TMS) derivative.

Drug/Drug Interactions with Oxycodone

Opioid analgesics may enhance the neuromuscular-blocking action of skeletal muscle relaxants and produce an increase in the degree of respiratory depression.

Patients receiving CNS depressants such as other opioid analgesics, general anesthetics, phenothiazines, other tranquilizers, centrally-acting anti-emetics, sedative-hypnotics or other CNS depressants (including alcohol) concomitantly with ENDODAN tablets may exhibit an additive CNS depression. When such combined therapy is contemplated, the dose of one or both agents should be reduced.

Agonist/antagonist analgesics (i.e., pentazocine, nalbuphine, naltrexone, and butorphanol) should be administered with caution to a patient who has received or is receiving a pure opioid agonist such as oxycodone. These agonist/antagonist analgesics may reduce the analgesic effect of oxycodone or may precipitate withdrawal symptoms.

Drug/Drug Interactions with Aspirin

Angiotensin Converting Enzyme (ACE) Inhibitors: The hyponatremic and hypotensive effects of ACE inhibitors may be diminished by the concomitant administration of aspirin due to its indirect effect on the renin-angiotensin conversion pathway.

Acetazolamide: Concurrent use of aspirin and acetazolamide can lead to high serum concentrations of acetazolamide (and toxicity) due to competition at the renal tubule for secretion.

Anticoagulant Therapy (Heparin and Warfarin): Patients on anticoagulation therapy are at increased risk for bleeding because of drug-drug interactions and the effect on platelets. Aspirin can displace warfarin from protein binding sites, leading to prolongation of both the prothrombin time and the bleeding time. Aspirin can increase the anticoagulant activity of heparin, increasing bleeding risk.

Anticonvulsants: Salicylate can displace protein-bound phenytoin and valproic acid, leading to a decrease in the total concentration of phenytoin and an increase in serum valproic acid levels.

Beta Blockers: The hypotensive effects of beta blockers may be diminished by the concomitant administration of aspirin due to inhibition of renal prostaglandins, leading to decreased renal blood flow, and salt and fluid retention.

Diuretics: The effectiveness of diuretics in patients with underlying renal or cardiovascular disease may be diminished by the concomitant administration of aspirin due to inhibition of renal prostaglandins, leading to decreased renal blood flow and salt and fluid retention.

Methotrexate: Aspirin may enhance the serious side and toxicity of methotrexate due to displacement from its plasma protein binding sites and/or reduced renal clearance.

Nonsteroidal Anti-inflammatory Drugs (NSAID's): The concurrent use of aspirin with other NSAID's should be avoided because this may increase bleeding or lead to decreased renal function. Aspirin may enhance the serious side effects and toxicity of ketorolac, due to displacement from its plasma protein binding sites and/or reduced renal clearance.

Oral Hypoglycemics Agents: Aspirin may increase the serum glucose-lowering action of insulin and sulfonylureas leading to hypoglycemia.

Uricosuric Agents: Salicylates antagonize the uricosuric action of probenecid or sulfinpyrazone.

Drug/Laboratory Test Interactions

Depending on the sensitivity/specificity and the test methodology, the individual components of ENDODAN tablets may cross-react with assays used in the preliminary detection of cocaine (primary urinary metabolite, benzoylecgonine) or marijuana (cannabinoids) in human urine. A more specific alternate chemical method must be used in order to obtain a confirmed analytical result. The preferred confirmatory method is gas chromatography/mass spectrometry (GC/MS). Moreover, clinical considerations and professional judgment should be applied to any drug-of-abuse test result, particularly when preliminary positive results are used.

Salicylates may increase the protein bound iodine (PBI) result by competing for the protein binding sites on pre-albumin and possibly thyroid-binding globulins.

Carcinogenesis, Mutagenesis, Impairment of Fertility

Carcinogenesis

Animal studies to evaluate the carcinogenic potential of oxycodone and aspirin have not been performed.

Mutagenesis

The combination of oxycodone and aspirin has not been evaluated for mutagenicity. Oxycodone alone was negative in a bacterial reverse mutation assay (Ames), an in vitro chromosome aberration assay with human lymphocytes without metabolic activation and an in vivo mouse micronucleus assay. Oxycodone was clastogenic in the human lymphocyte chromosomal assay in the presence of metabolic activation and in the mouse lymphoma assay with or without metabolic activation. Aspirin induced chromosome aberrations in cultured human fibroblasts.

Fertility

Animal studies to evaluate the effects of oxycodone on fertility have not been performed. Aspirin has been shown to inhibit ovulation in rats.

Pregnancy

Teratogenic Effects
Oxycodone: Pregnancy Category B

Reproduction studies in rats and rabbits demonstrated that oral administration of oxycodone was not teratogenic or embryo-fetal toxic.

Aspirin: Pregnancy Category D (see PRECAUTIONS)

Salicylates readily cross the placenta and by inhibiting prostaglandin synthesis, may cause constriction of ductus arteriosus resulting in pulmonary hypertension and increased fetal mortality and, possibly other untoward fetal effects. Aspirin use in pregnancy can also result in alteration in maternal and neonatal hemostasis mechanisms. Maternal aspirin use during later stages of pregnancy may cause low birth weight, increased incidence of intracranial hemorrhage in premature infants, stillbirths and neonatal death. Use during pregnancy, especially in the third trimester, should be avoided.

Safe use of ENDODAN (Oxycodone and Aspirin Tablets, USP) in pregnancy has not been established relative to possible adverse effects on fetal development. Therefore, ENDODAN tablets should not be used in pregnant women unless, in the judgment of the physician, the potential benefits outweigh the possible hazards.

Nonteratogenic Effects

Opioids can cross the placental barrier and have the potential to cause neonatal respiratory depression. Opioid use during pregnancy may result in a physically drug-dependent fetus. After birth, the neonate may suffer severe withdrawal symptoms. Aspirin may produce anemia, ante- or postpartum hemorrhage, prolonged gestation and labor, and oligohydramnios.

Labor and Delivery

ENDODAN tablets are not recommended for use in women during and immediately prior to labor and delivery due to its potential effects on respiratory function in the newborn. Aspirin should be avoided one week prior to and during labor and delivery because it can result in excessive blood loss at delivery. Prolonged gestation and prolonged labor due to prostaglandin inhibition have been reported.

Nursing Mothers

Ordinarily, nursing should not be undertaken while a patient is receiving ENDODAN tablets because of the possibility of sedation and/or respiratory depression in the infant. Oxycodone is excreted in breast milk in low concentrations, and there have been rare reports of somnolence and lethargy in babies of nursing mothers taking an oxycodone/acetaminophen product. Salicylic acid has also been detected in breast milk. Adverse effects on platelet function in the nursing infant exposed to aspirin in breast milk may be a potential risk. Furthermore, the risk of Reye Syndrome caused by salicylate in breast milk is unknown. Because of the potential for serious adverse reactions in nursing infants, a decision should be made whether to discontinue nursing or to discontinue the drug, taking into account the potential benefits to the woman and the possible hazards to the nursing infant.

Pediatric Use

ENDODAN tablets should not be administered to pediatric patients. Reye Syndrome is a rare but serious disease which can follow flu or chicken pox in children and teenagers. While the cause of Reye Syndrome is unknown, some reports claim aspirin (or salicylates) may increase the risk of developing this disease.

Geriatric Use

Special precaution should be given when determining the dosing amount and frequency of ENDODAN tablets for geriatric patients, since clearance of oxycodone may be slightly reduced in this patient population when compared to younger patients.

Hepatic Impairment

In a pharmacokinetic study of oxycodone in patients with end-stage liver disease, oxycodone plasma clearance decreased and the elimination half-life increased. Care should be exercised when oxycodone is used in patients with hepatic impairment.

Renal Impairment

In a study of patients with end stage renal impairment, mean elimination half-life was prolonged in uremic patients due to increased volume of distribution and reduced clearance. Oxycodone should be used with caution in patients with renal impairment.

ADVERSE REACTIONS

Serious adverse reactions that may be associated with ENDODAN tablet use include respiratory depression, apnea, respiratory arrest, circulatory depression, hypotension, and shock (see OVERDOSAGE).

The most frequently observed non-serious adverse reactions include lightheadedness, dizziness, drowsiness or sedation, nausea, and vomiting. These effects seem to be more prominent in ambulatory than in nonambulatory patients, and some of these adverse reactions may be alleviated if the patient lies down. Other adverse reactions include euphoria, dysphoria, constipation and pruritus.

Aspirin may increase the likelihood of hemorrhage due to its effect on the gastric mucosa and platelet function. Furthermore, aspirin has the potential to cause anaphylaxis in hypersensitive patients as well as angioedema especially in patients with chronic urticaria. Other adverse reactions due to aspirin use include anorexia, reversible hepatotoxicity, leukopenia, thrombocytopenia, purpura, decreased plasma iron concentration, and shortened erythrocyte survival time.

Other adverse reactions obtained from postmarketing experiences with ENDODAN tablets are listed by organ system and in decreasing order of severity and/or frequency as follows:

Body as a Whole

allergic reaction, malaise, asthenia, headache, anaphylaxis, fever, hypothermia, thirst, increased sweating, accident, accidental overdose, non-accidental overdose.

Cardiovascular

tachycardia, dysrhythmias, hypotension, orthostatic hypotension, bradycardia, palpitations

Central and Peripheral Nervous System

stupor, paresthesia, agitation, cerebral edema, coma, confusion, dizziness, headache, subdural or intracranial hemorrhage, lethargy, seizures, anxiety, mental impairment

Fluid and Electrolyte

dehydration, hyperkalemia, metabolic acidosis, respiratory alkalosis

Gastrointestinal

hemorrhagic gastric/duodenal ulcer, gastric/peptic ulcer, dyspepsia, abdominal pain, diarrhea, eructation, dry mouth, gastrointestinal bleeding, intestinal perforation, nausea, vomiting, transient elevations of hepatic enzymes, hepatitis, Reye syndrome, pancreatitis, intestinal obstruction, ileus

Hearing and Vestibular

hearing loss, tinnitus. Patients with high frequency loss may have difficulty perceiving tinnitus. In these patients, tinnitus cannot be used as a clinical indicator of salicylism.

Hematologic

unspecified hemorrhage, purpura, reticulocytosis, prolongation of prothrombin time, disseminated intravascular coagulation, ecchymosis, thrombocytopenia.

Hypersensitivity

acute anaphylaxis, angioedema, asthma, bronchospasm, laryngeal edema, urticaria, anaphylactoid reaction

Metabolic and Nutritional

hypoglycemia, hyperglycemia, acidosis, alkalosis

Musculoskeletal

rhabdomyolysis

Ocular

miosis, visual disturbances, red eye.

Psychiatric

drug dependence, drug abuse, somnolence, depression, nervousness, hallucination

Reproductive

prolonged pregnancy and labor, stillbirths, lower birth weight infants, antepartum and postpartum bleeding, closure of patent ductus arteriosis

Respiratory System

bronchospasm, dyspnea, hyperpnea, pulmonary edema, tachypnea, aspiration, hypoventilation, laryngeal edema

Skin and Appendages

urticaria, rash, flushing

Urogenital

interstitial nephritis, papillary necrosis, proteinuria, renal insufficiency and failure, urinary retention

OVERDOSAGE

Signs and Symptoms

Serious overdose with ENDODAN (Oxycodone and Aspirin Tablets, USP) is characterized by signs and symptoms of opioid and salicylate overdose. Oxycodone overdosage can be manifested by respiratory depression (a decrease in respiratory rate and/or tidal volume, Cheyne-Stokes respiration, cyanosis), extreme somnolence progressing to stupor or coma, skeletal muscle flaccidity, cold and clammy skin, pupillary constriction (pupils may be dilated in the setting of hypoxia), and sometimes bradycardia and hypotension. In severe overdosage, apnea, circulatory collapse, cardiac arrest and death may occur. Early signs of acute aspirin (salicylate) overdose including tinnitus occur at plasma concentrations approaching 200 mcg/mL. Plasma concentrations of aspirin above 300 mcg/mL are toxic. Severe toxic effects are associated with levels above 400 mcg/mL. A single lethal dose of aspirin in adults is not known with certainty but death may be expected at 30 g. For real or suspected overdose, a Poison Control Center should be contacted immediately.

In acute salicylate overdose, severe acid-base and electrolyte disturbances may occur and are complicated by hyperthermia and dehydration, and coma. Respiratory alkalosis occurs early while hyperventilation is present, but is quickly followed by metabolic acidosis. Serious symptoms such as depression, coma, and respiratory failure progress rapidly.

Salicylism (chronic salicylate toxicity) may be noted by symptoms such as dizziness, tinnitus, difficulty hearing, nausea, vomiting, diarrhea, and mental confusion. More severe salicylism may result in respiratory alkalosis.

Treatment

Primary attention should be given to the reestablishment of adequate respiratory exchange through provision of a patent airway and the institution of assisted or controlled ventilation. Supportive measures (including oxygen, intravenous fluids, and vasopressors) should be employed in the management of circulatory shock and pulmonary edema accompanying overdose as indicated. Cardiac arrest or arrhythmias may require cardiac massage or defibrillation. Treatment of acid-base disturbances and electrolyte disorders is also important. Because of the concern over salicylate toxicity, acid-base status should be followed closely with serial blood gas and serum pH determinations.

The opioid antagonist naloxone hydrochloride is a specific antidote against respiratory depression which may result from overdosage or unusual sensitivity to opioids including oxycodone. Therefore, an appropriate dose of naloxone hydrochloride should be administered (usual initial adult dose 0.4 mg-2 mg) preferably by the intravenous route, simultaneously with efforts at respiratory resuscitation. Since the duration of action of oxycodone may exceed that of the antagonist, the patient should be kept under continued surveillance and repeated doses of the antagonist should be administered as needed to maintain adequate respiration. Opioid antagonists should not be administered in the absence of clinically significant respiratory or circulatory depression secondary to oxycodone overdose. In patients who are physically dependent on any opioid agonist including oxycodone, an abrupt or complete reversal of opioid effects may precipitate an acute abstinence syndrome. The severity of the withdrawal syndrome produced will depend on the degree of physical dependence and the dose of the antagonist administered. Please see the prescribing information for the specific opioid antagonist for details of their proper use.

Gastric emptying and/or lavage may be useful in removing unabsorbed drug. This procedure is recommended as soon as possible after ingestion, even if the patient has vomited spontaneously. After lavage and/or emesis, administration of activated charcoal, as a slurry, is beneficial, if less than three hours have passed since ingestion. Charcoal adsorption should not be employed prior to lavage and emesis.

In severe cases of salicylate overdose, hyperthermia and hypovolemia are the major immediate threats to life. Children should be sponged with tepid water. Replacement fluid should be administered intravenously and augmented with correction of acidosis. Plasma electrolytes and pH should be monitored to promote alkaline diuresis of salicylate if renal function is normal. Infusion of glucose may be required to control hypoglycemia. With more severe acute toxicity respiratory alkalosis may occur.

Hemodialysis and peritoneal dialysis can be performed to reduce the body content of aspirin. In patients with renal insufficiency or in cases of life-threatening salicylate intoxication dialysis is usually required. Exchange transfusion may be indicated in infants and young children.

In case of real or suspected overdose, a poison control center should be consulted for the treatment of salicylism.

The toxicity of oxycodone and aspirin in combination is unknown.

DOSAGE AND ADMINISTRATION

Dosage should be adjusted according to the severity of the pain and the response of the patient. It may occasionally be necessary to exceed the usual dosage recommended below in cases of more severe pain or in those patients who have become tolerant to the analgesic effect of opioids. If pain is constant, the opioid analgesic should be given at regular intervals on an around-the-clock schedule. ENDODAN tablets are given orally.

The usual dosage is one tablet every 6 hours as needed for pain. The maximum daily dose of aspirin should not exceed 4 grams or 12 tablets.

Cessation of Therapy

In patients treated with ENDODAN tablets for more than a few weeks who no longer require therapy, doses should be tapered gradually to prevent signs and symptoms of withdrawal in the physically dependent patient.

DRUG ABUSE AND DEPENDENCE

ENDODAN tablets are a Schedule II controlled substance. Oxycodone is a mu-agonist opioid with an abuse liability similar to morphine. Oxycodone, like morphine and other opioids used in analgesia, can be abused and is subject to criminal diversion.

Drug addiction is defined as an abnormal, compulsive use, use for non-medical purposes of a substance despite physical, psychological, occupational or interpersonal difficulties resulting from such use, and continued use despite harm or risk of harm. Drug addiction is a treatable disease, utilizing a multi-disciplinary approach, but relapse is common. Opioid addiction is relatively rare in patients with chronic pain but may be more common in individuals who have a past history of alcohol or substance abuse or dependence. Pseudoaddiction refers to pain relief seeking behavior of patients whose pain is poorly managed. It is considered an iatrogenic effect of ineffective pain management. The health care provider must assess continuously the psychological and clinical condition of a pain patient in order to distinguish addiction from pseudoaddiction and thus, be able to treat the pain adequately.

Physical dependence on a prescribed medication does not signify addiction. Physical dependence involves the occurrence of a withdrawal syndrome when there is sudden reduction or cessation in drug use or if an opiate antagonist is administered. Physical dependence can be detected after a few days of opioid therapy. However, clinically significant physical dependence is only seen after several weeks of relatively high dosage therapy. In this case, abrupt discontinuation of the opioid may result in a withdrawal syndrome. If the discontinuation of opioids is therapeutically indicated, gradual tapering of the drug over a 2-week period will prevent withdrawal symptoms. The severity of the withdrawal syndrome depends primarily on the daily dosage of the opioid, the duration of therapy and medical status of the individual.

The withdrawal syndrome of oxycodone is similar to that of morphine. This syndrome is characterized by yawning, anxiety, increased heart rate and blood pressure, restlessness, nervousness, muscle aches, tremor, irritability, chills alternating with hot flashes, salivation, anorexia, severe sneezing, lacrimation, rhinorrhea, dilated pupils, diaphoresis, piloerection, nausea, vomiting, abdominal cramps, diarrhea and insomnia, and pronounced weakness and depression.

“Drug-seeking” behavior is very common in addicts and drug abusers. Drug-seeking tactics include emergency calls or visits near the end of office hours, refusal to undergo appropriate examination, testing or referral, repeated “loss” of prescriptions, tampering with prescriptions and reluctance to provide prior medical records or contact information for other treating physician(s). “Doctor shopping” to obtain additional prescriptions is common among drug abusers and people suffering from untreated addiction.

Abuse and addiction are separate and distinct from physical dependence and tolerance. Physicians should be aware that addiction may not be accompanied by concurrent tolerance and symptoms of physical dependence in all addicts. In addition, abuse of opioids can occur in the absence of true addiction and is characterized by misuse for non-medical purposes, often in combination with other psychoactive substances. Oxycodone, like other opioids, has been diverted for non-medical use. Careful record-keeping of prescribing information, including quantity, frequency, and renewal requests is strongly advised.

Proper assessment of the patient, proper prescribing practices, periodic re-evaluation of therapy, and proper dispensing and storage are appropriate measures that help to limit abuse of opioid drugs.

Like other opioid medications, ENDODAN tablets are subject to the Federal Controlled Substances Act. After chronic use, ENDODAN tablets should not be discontinued abruptly when it is thought that the patient has become physically dependent on oxycodone.

Interactions with Alcohol and Drugs of Abuse

Oxycodone may be expected to have additive effects when used in conjunction with alcohol, other opioids, or illicit drugs that cause central nervous system depression.

HOW SUPPLIED

ENDODAN (oxycodone and aspirin tablets, USP), supplied as a yellow round tablet, with one face scored and the other debossed with “Endo” and “610”.

Available in:

Bottles of 100 NDC 60951-310-70

Store at 25°C (77°F); excursions permitted to 15°-30°C (59°-86°F). [See USP Controlled Room Temperature.]

Dispense in a tight, light-resistant container as defined in the USP, with a child-resistant closure (as required).

DEA Order Form Required.

Manufactured for:

Endo Pharmaceuticals Inc.

Chadds Ford, Pennsylvania 19317

ENDODAN® is a Registered Trademark of Endo Pharmaceuticals

© 2009 Endo Pharmaceuticals

Printed in U.S.A. 2005701/September, 2009